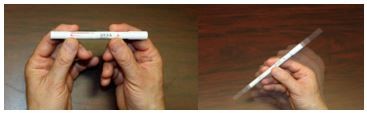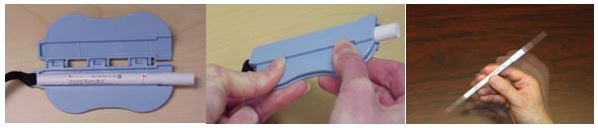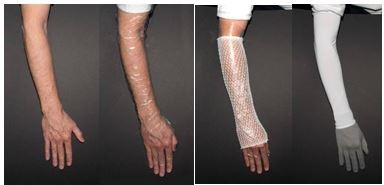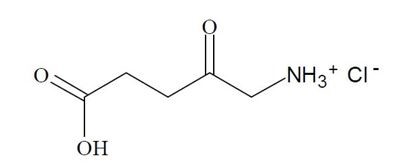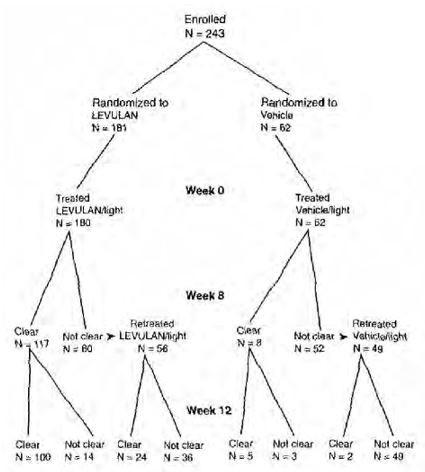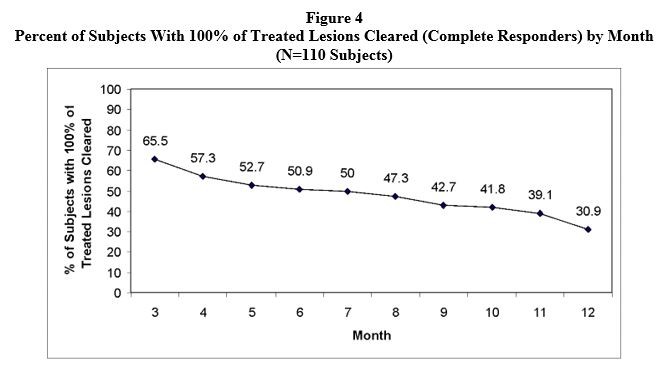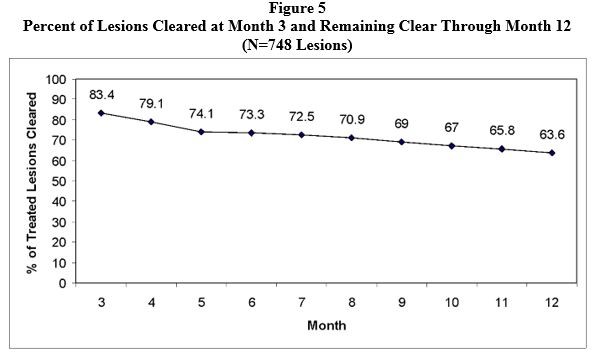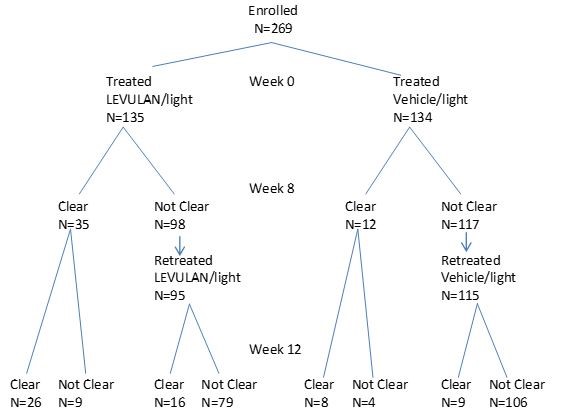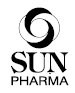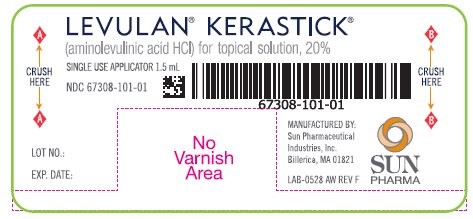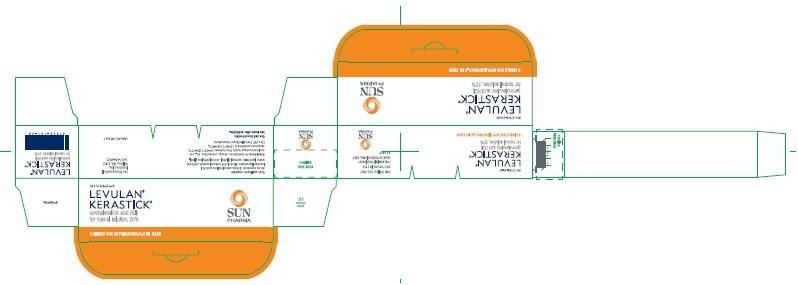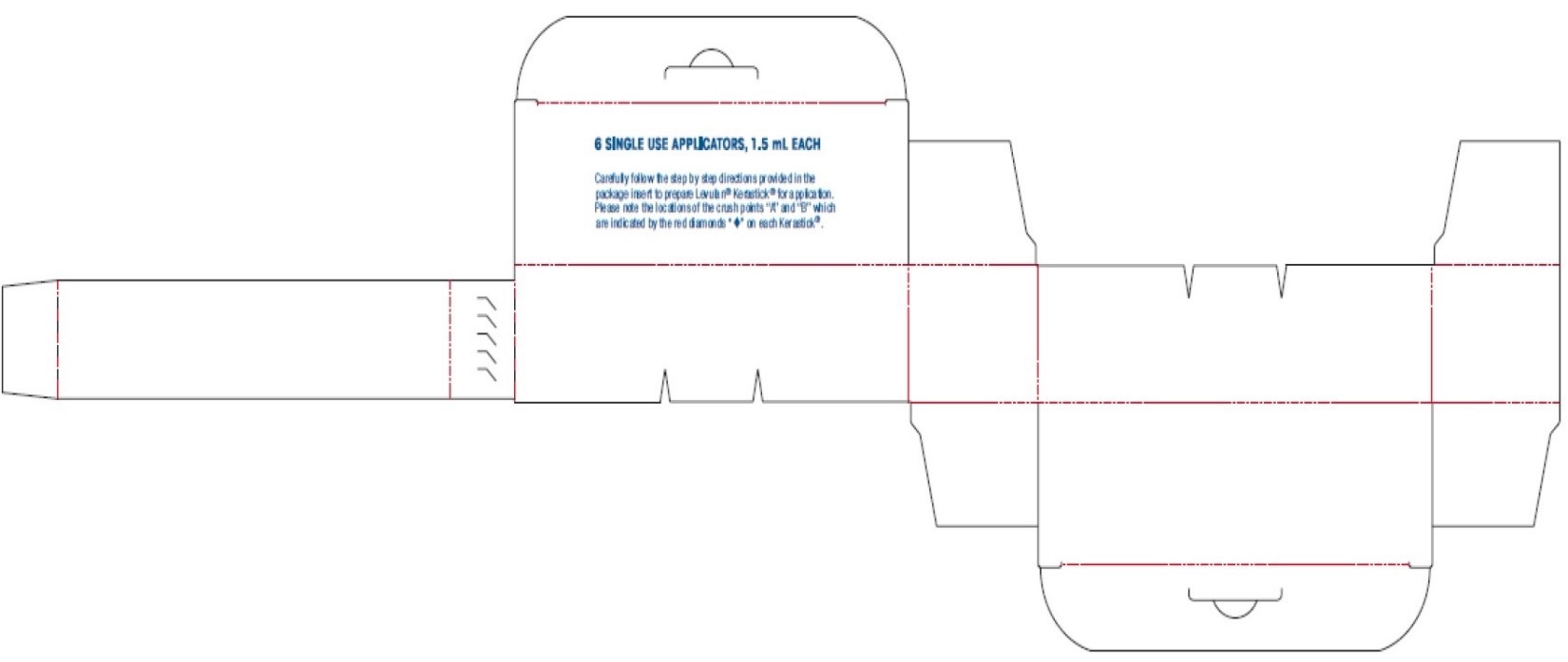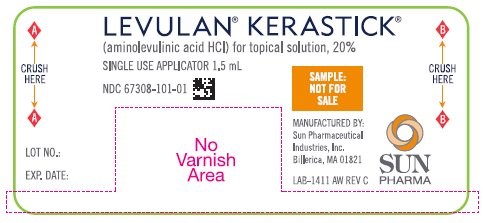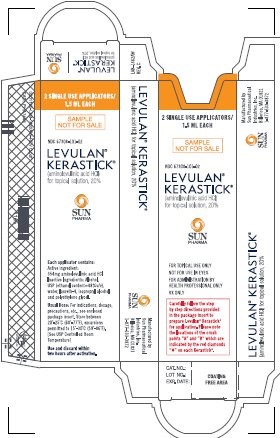 DRUG LABEL: LEVULAN KERASTICK
NDC: 67308-101 | Form: KIT | Route: TOPICAL
Manufacturer: Sun Pharmaceutical Industries, Inc
Category: prescription | Type: HUMAN PRESCRIPTION DRUG LABEL
Date: 20240912

ACTIVE INGREDIENTS: AMINOLEVULINIC ACID HYDROCHLORIDE 354 mg/1.5 mL
INACTIVE INGREDIENTS: ALCOHOL; WATER; LAURETH-4; ISOPROPYL ALCOHOL; POLYETHYLENE GLYCOL, UNSPECIFIED

HIGHLIGHTS OF PRESCRIBING INFORMATION

These highlights do not include all the information needed to use LEVULAN®KERASTICK®safely and effectively. See full prescribing information for LEVULAN KERASTICK.
LEVULAN KERASTICK (aminolevulinic acid HCl) for Topical Solution, 20%
Initial U.S. Approval: 1999

RECENT MAJOR CHANGES

Indications and Usage (1) | 03/2018
Dosage and Administration (2) | 03/2018
Warning and Precautions, Irritation (5.2, 5.3) | 03/2018
Warning and Precautions (5.1) | 04/2018

1 INDICATIONS AND USAGE

LEVULAN KERASTICK for topical solution, a porphyrin precursor, plus blue light illumination using the BLU-U Blue Light Photodynamic Therapy Illuminator is indicated for photodynamic therapy (treatment) of minimally to moderately thick actinic keratoses of the face or scalp, or actinic keratoses of the upper extremities. (1)

2 DOSAGE AND ADMINISTRATION

- LEVULAN KERASTICK photodynamic therapy is a two-stage process for administration by a health care provider.(2.1)
- Apply the drug product to the target lesions. (2.1)
- Illuminate with blue light using the BLU-U®Blue Light Photodynamic Therapy Illuminator after the incubation time of(2.2):
  - 14 to 18 hours for scalp or face
  - 3 hours for upper extremities, with occlusion
- LEVULAN KERASTICK photodynamic therapy may be repeated a second time for lesions that have not completely resolved after 8 weeks (2.1)
- For topical use only. (2.1)
- See full prescribing information for complete dosage and administration instruction. (2)
- See BLU-U user manual for detailed lamp safety and operating instructions. (2.2)

3 DOSAGE FORMS AND STRENGTHS

After mixture, topical solution contains 20% aminolevulinic acid hydrochloride (ALA HCl) by weight in a plastic applicator device. (3)

4 CONTRAINDICATIONS

- Cutaneous photosensitivity at wavelengths of 400-450 nm. (4)
- Porphyria or known allergies to porphyrins. (4)
- Sensitivity to any of the components of the LEVULAN KERASTICK. (4)

5 WARNINGS AND PRECAUTIONS

- Transient amnestic episodes have been reported during postmarketing use of LEVULAN KERASTICK in combination with BLU-U Blue Light Photodynamic Therapy Illuminator. Inform patients and their caregivers that LEVULAN KERASTICK in combination with PDT may cause transient amnestic episodes. Advise them to contact the healthcare provider if the patient develops amnesia after treatment. (5.1)
- Avoid exposure of the photosensitive actinic keratoses to sunlight or bright indoor light prior to blue light treatment. Protect treated lesions from sunlight exposure. Sunscreens will not protect the patient against photosensitivity reactions. (5.2)
- The LEVULAN KERASTICK for topical solution should be used by a qualified health professional. To avoid unintended photosensitivity, LEVULAN KERASTICK topical solution should be applied to no more than 5 mm of perilesional skin surrounding each target actinic keratosis lesion. (5.2)
- Irritation may be experienced if this product is applied to eyes or mucous membranes. Do not apply to the eyes or to mucous membranes. Excessive irritation may be experienced if this product is applied under occlusion longer than 3 hours. (5.3)

6 ADVERSE REACTIONS

The most common local adverse reactions (incidence ≥ 10%) were erythema, edema, stinging/burning, scaling/crusting, itching, erosion, hypo/hyperpigmentation, oozing/vesiculation/crusting, scaling and dryness. (6.1)

To report SUSPECTED ADVERSE REACTIONS, contact Sun Dermatology at 877-533-3872 or FDA at 1-800-FDA-1088 or www.fda.gov/medwatch.

7 DRUG INTERACTIONS

Concomitant use of other known photosensitizing agents such as St. John’s wort, griseofulvin, thiazide diuretics, sulfonylureas, phenothiazines, sulfonamides and tetracyclines might increase the photosensitivity reaction. (7)

FULL PRESCRIBING INFORMATION

1 INDICATIONS AND USAGE

The LEVULAN KERASTICK for topical solution plus blue light illumination using the BLU-U Blue Light Photodynamic Therapy Illuminator is indicated for the treatment of minimally to moderately thick actinic keratoses of the face, scalp, or upper extremities.

2 DOSAGE AND ADMINISTRATION

2.1 Preparation and Administration Overview

After mixing, the LEVULAN KERASTICK topical solution 20% is intended for direct application to individual lesions diagnosed as actinic keratoses and not to perilesional skin. This product is not intended for application by patients or unqualified medical personnel. Application should involve lesions on the scalp, face or upper extremities; multiple lesions can be treated within a treatment region, but multiple treatment regions should not be treated simultaneously.

The recommended treatment frequency is: one application of the LEVULAN KERASTICK topical solution and one dose of illumination per treatment region per 8-week treatment session. Each individual LEVULAN KERASTICK applicator should be used for only one patient.

LEVULAN KERASTICK photodynamic therapy for actinic keratoses is a two-stage process involving application of the LEVULAN KERASTICK topical solution to the target lesions and then illumination with blue light using the BLU-U Blue Light Photodynamic Therapy Illuminator after 3 hours for upper extremity lesions or after 14-18 hours for face or scalp lesions.

TABLE 1 Schedule for LEVULAN KERASTICK Photodynamic Therapy
LEVULAN KERASTICK topical solution application | Time window^1for Blue Light Illumination for face or scalp | Time window^2for Blue Light Illumination for upper extremities
6 am | 8 pm to Midnight | 9 am
7 am | 9 pm to 1 am | 10 am
8 am | 10 pm to 2 am | 11 am
9 am | 11 pm to 3 am | 12 Noon
10 am | Midnight to 4 am | 1 pm
11 am | 1 am to 5 am | 2 pm
12 pm | 2 am to 6 am | 3 pm
1 pm | 3 am to 7 am | 4 pm
2 pm | 4 am to 8 am | 5 pm
3 pm | 5 am to 9 am | 6 pm
4 pm | 6 am to 10 am | 7 pm
5 pm | 7 am to 11 am | 8 pm
6 pm | 8 am to Noon | 9 pm
7 pm | 9 am to 1 pm | 10 pm
8 pm | 10 am to 2 pm | 11 pm
9 pm | 11 am to 3 pm | 12 Midnight
10 pm | Noon to 4 pm | 1 am
^1The incubation time is 14-18 hours for actinic keratosis lesions on the face or scalp.
^2 The incubation time is 3 hours for actinic keratosis lesions on the upper extremities.

If for any reason the patient cannot be given BLU-U Blue Light Photodynamic Therapy Illuminator treatment during the prescribed time after applying LEVULAN KERASTICK topical solution, he or she may nonetheless experience sensations of stinging and/or burning if the photosensitized actinic keratoses are exposed to sunlight or prolonged or intense light at that time. Advise the patient to wear appropriate protective apparel (e.g., wide-brimmed hat, long sleeve shirt, gloves) to shade the treated actinic keratoses from sunlight or other bright light sources until at least 40 hours after the application of LEVULAN KERASTICK topical solution. Advise the patient to reduce light exposure if the sensations of stinging and/or burning are experienced.

LEVULAN KERASTICK photodynamic therapy may be repeated a second time for lesions that have not completely resolved 8 weeks after the initial treatment.

2.2 Dosage and Administration Instructions

Step A - Treatment of Actinic Keratoses with LEVULAN KERASTICK Topical Solution

Preparation of Lesions

Actinic keratoses targeted for treatment should be clean and dry prior to application of LEVULAN KERASTICK Topical Solution.

Preparation of LEVULAN KERASTICK topical solution

The LEVULAN KERASTICK applicator consists of a plastic tube containing two sealed glass ampules and an applicator tip. One ampule contains 1.5 mL of solution vehicle. The other ampule contains aminolevulinic acid HCl as a dry solid. LEVULAN KERASTICK topical solution is prepared by crushing the glass ampoules and mixing the contents together.

The LEVULAN KERASTICK topical solution can be prepared either manually, or using the optional KERASTICK KRUSHER™. These methods are illustrated below.

Figure 1: Manual Preparation:

1. Hold the LEVULAN KERASTICK applicator with cap point up. Crush the bottom ampule containing the solution vehicle by applying finger pressure to Position A on the cardboard sleeve.
2. Crush the top ampule containing the ALA HCl powder by applying finger pressure to Position B on the cardboard sleeve. To ensure both ampules are crushed continue crushing the applicator downward, applying finger pressure to Position A. Shake the LEVULAN KERASTICK applicator gently for at least 30 seconds to completely dissolve the drug powder in the solution vehicle.

Figure 2: Optional KERASTICK KRUSHER Preparation:

1. Open the KERASTICK KRUSHER and properly position one LEVULAN KERASTICK applicator into the KRUSHER making sure to orient the LEVULAN KERASTICK label “A” with the KRUSHER “A”. Firmly seat the LEVULAN KERASTICK applicator against the closed end of the KRUSHER (cap should be at open end).
2. Once positioned properly, close and firmly press the top and bottom handles together until the top and bottom handles touch one another along their length. A distinct crushing sound is made during this process. Ensure KRUSHER handles meet.
3. Remove the LEVULAN KERASTICK applicator from the KRUSHER and shake the LEVULAN KERASTICK applicator gently for at least 30 seconds to completely dissolve the drug powder in the solution vehicle.

The LEVULAN KERASTICK topical solution must be used within two (2) hours of activation. If the solution is not completely applied within 2 hours of the activation, discard the applicator. If needed, use a new LEVULAN KERASTICK applicator.

Application of LEVULAN KERASTICK topical solution

Application of LEVULAN KERASTICK topical solution to Face or Scalp Lesions:

Following solution admixture, remove the cap from the LEVULAN KERASTICK applicator. The dry applicator tip should be dabbed on a gauze pad until uniformly wet with solution. Apply the solution directly to the target lesions by dabbing gently with the wet applicator tip. Enough solution should be applied to uniformly wet the lesion surface, including the edges without excess running or dripping. Once the initial application has dried, apply again in the same manner.

Do not apply the LEVULAN KERASTICK topical solution to the periorbital area or allow it to contact ocular or mucosal surfaces.

Photosensitization of the treated lesions will take place over the next 14-18 hours. The actinic keratoses should not be washed during this time. The patient should be advised to wear a wide-brimmed hat or other protective apparel to shade the treated actinic keratoses from sunlight or other bright light sources until BLU-U Blue Light Photodynamic Therapy Illuminator treatment. The patient should be advised to reduce light exposure if the sensations of stinging and/or burning are experienced.

At the visit for light illumination before treatment, the actinic keratoses treated with the LEVULAN KERASTICK topical solution should be gently rinsed with water and patted dry.

For Lesions on the Upper Extremities

Following solution mixture, remove the cap from the LEVULAN KERASTICK applicator. The dry applicator tip should be dabbed on a gauze pad until uniformly wet with solution. Apply the solution directly to the target lesions by dabbing gently with the wet applicator tip. Enough solution should be applied to uniformly wet the lesion surface, including the edges without excess running or dripping.

Occlude the upper extremity with low density polyethylene plastic wrap and hold in place with an elastic net dressing.
Figure 3: Method of Occlusion for Upper Extremities

The patient should wear a long-sleeved shirt and/or gloves or other protective apparel to shade the treated actinic keratoses from sunlight or other bright light sources until BLU-U Blue Light Photodynamic Therapy Illuminator treatment. Photosensitization of the treated lesions will take place over the next 3 hours. The actinic keratoses should not be washed during this time. Remove the occlusive dressing prior to light treatment and gently rinse the treated area(s) with water and pat dry before light illumination.

Step B - Administration of BLU-U Treatment:

LEVULAN KERASTICK is not intended for use with any device other than the BLU-U Blue Light Photodynamic Therapy Illuminator. Use of LEVULAN KERASTICK without subsequent BLU-U Blue Light Photodynamic Therapy Illuminator illumination is not recommended.

Photoactivation of actinic keratoses treated with LEVULAN KERASTICK topical solution is accomplished with illumination from the BLU-U Blue Light Photodynamic Therapy Illuminator. A 1000 second (16 minutes 40 seconds) exposure is required to provide a 10 J/cm^2light dose. During light treatment, both patients and medical personnel should be provided with blue blocking protective eyewear, as specified in the BLU-U Blue Light Photodynamic Therapy Illuminator Operating Instructions. Please refer to the BLU-U Blue Light Photodynamic Therapy Illuminator Operating Instructions for further information on conducting the light treatment. Patients should be advised that transient stinging and/or burning at the target lesion sites occurs during the period of light exposure.

If blue light treatment with the BLU-U Blue Light Photodynamic Therapy Illuminator is interrupted or stopped for any reason, it should not be restarted and the patient should be advised to protect the treated lesions from exposure to sunlight or prolonged or intense light for at least 40 hours after applying the LEVULAN KERASTICK topical solution.

For patients with facial lesions:

1. The BLU-U Blue Light Photodynamic Therapy Illuminator is positioned so that the base is slightly above the patient’s shoulder, parallel to the patient’s face.
2. The BLU-U is positioned around the patient’s head so the entire surface area to be treated lies between 2” and 4” from the BLU-U surface:
  a) The patient’s nose should be no closer than 2” from the surface;
  b) The patient’s forehead and cheeks should be no further than 4” from the surface;
  c) The sides of the patient’s face and the patient’s ears should be no closer than 2” from the BLU-U surface.

For patients with scalp lesions:

1. The knobs on either side of the BLU-U are loosened and the BLU-U is rotated to a horizontal position.
2. The BLU-U is positioned around the patient’s head so the entire surface area to be treated lies between 2” and 4” from the BLU-U surface:
  a) The patient’s scalp should be no closer than 2” from the surface;
  b) The patient’s scalp should be no further than 4” from the surface;
  c) The sides of the patient’s face and the patient’s ears should be no closer than 2” from the BLU-U surface.

For patients with upper extremity lesions:

1. The knobs on either side of the BLU-U Blue Light Photodynamic Therapy Illuminator are loosened and the light is rotated to a horizontal position.
2. The BLU-U Blue Light Photodynamic Therapy Illuminator is positioned around the upper extremity so the entire surface area to be treated lies between 2” and 4” from the BLU-U surface. A table may be used to support the upper extremities during light treatment.

3 DOSAGE FORMS AND STRENGTHS

For topical solution: 354 mg of aminolevulinic acid hydrochloride as a powder in a plastic applicator device. Upon mixture, LEVULAN KERASTICK is a topical solution containing 20% aminolevulinic acid hydrochloride (ALA HCl) by weight.

4 CONTRAINDICATIONS

The LEVULAN KERASTICK for topical solution plus blue light illumination using the BLU-U Blue Light Photodynamic Therapy Illuminator is contraindicated in patients with:

- Cutaneous photosensitivity at wavelengths of 400-450 nm [see Warnings and Precautions (5.2)]
- Porphyria or known allergies to porphyrins [see Warnings and Precautions (5.2)]
- Known sensitivity to any of the components of the LEVULAN KERASTICK.

5 WARNINGS AND PRECAUTIONS

5.1 Transient Amnestic Episodes

Transient amnestic episodes have been reported during postmarketing use of LEVULAN KERASTICK in combination with BLU-U Blue Light Photodynamic Therapy Illuminator. Inform patients and their caregivers that LEVULAN KERASTICK in combination with PDT may cause transient amnestic episodes. Advise them to contact the healthcare provider if the patient develops amnesia after treatment.

5.2 Photosensitivity

After LEVULAN KERASTICK topical solution has been applied, the treatment site will become photosensitive and patients should avoid exposure of the photosensitive treatment sites to sunlight or bright indoor light (e.g., examination lamps, operating room lamps, tanning beds, or lights at close proximity) for 40 hours. Exposure may result in a stinging and/or burning sensation and may cause erythema and/or edema of the lesions.

Therefore, before exposure to sunlight, patients should protect treated lesions from the sun by wearing a wide-brimmed hat or similar head covering of light-opaque material, and/or a long-sleeved shirt and/or gloves. Sunscreens will not protect against photosensitivity reactions caused by visible light. It has not been determined if perspiration can spread the LEVULAN KERASTICK topical solution outside the treatment site to the eye or surrounding skin.

Application of LEVULAN KERASTICK topical solution to perilesional areas of photodamaged skin of the face, scalp or upper extremities may result in photosensitization. Upon exposure to activating light from the BLU-U, such photosensitized skin may produce a stinging and/or burning sensation and may become erythematous and/or edematous in a manner similar to that of actinic keratoses treated with LEVULAN KERASTICK Photodynamic Therapy. Because of the potential for skin to become photosensitized, the LEVULAN KERASTICK topical solution should be used by a qualified health professional to apply drug to no more than 5mm of perilesional skin surrounding the target actinic keratosis lesions.

If for any reason the patient cannot return for blue light treatment during the prescribed period after applying LEVULAN KERASTICK topical solution, the patient should call the doctor. The patient should also continue to avoid exposure of the photosensitized lesions to sunlight or prolonged or intense light for at least 40 hours. If stinging and/or burning is noted, exposure to light should be reduced.

5.3 Irritation

The LEVULAN KERASTICK topical solution contains alcohol and is intended for topical use only. Irritation may be experienced if this product is applied to eyes or mucous membranes. Do not apply to the eyes or to mucous membranes. Excessive irritation may be experienced if this product is applied under occlusion longer than 3 hours.

5.4 Coagulation Defects

The LEVULAN KERASTICK for topical solution has not been tested on patients with inherited or acquired coagulation defects.

6 ADVERSE REACTIONS

The following adverse reactions are discussed in greater detail in the other sections of the labeling:

- Transient Amnestic Episodes [see Warnings and Precautions (5.1)]
- Increased Photosensitivity [see Warnings and Precautions (5.2)]
- Irritation [see Warnings and Precautions (5.3)]
- Coagulation defects [see Warnings and Precautions (5.4)]

6.1 Clinical Trial Experience

Because clinical trials are conducted under widely varying conditions, adverse reaction rate observed in the clinical trials of a drug cannot be directly compared to rates in the clinical trials of another drug and may not reflect the rates observed in practice.

In clinical trials, no non-cutaneous adverse events were found to be consistently associated with LEVULAN KERASTICK photodynamic therapy.

Photodynamic Therapy Response:The constellation of transient local symptoms of stinging and/or burning, itching, erythema and edema as a result of LEVULAN KERASTICK photodynamic therapy (PDT) was observed in all clinical trials for actinic keratoses treatment. Stinging and/or burning subsided between 1 minute and 24 hours after the BLU-U Blue Light Photodynamic Therapy Illuminator was turned off, and appeared qualitatively similar to that perceived by patients with erythropoietic protoporphyria upon exposure to sunlight. There was no clear drug dose or light dose dependent change in the incidence or severity of stinging and/or burning.

Local skin reactions at the application site were observed in 99% of subjects treated with LEVULAN KERASTICK topical solution and BLU-U Blue Light Photodynamic Therapy Illuminator. The most common local adverse reactions (incidence ≥ 10%) were application site stinging/burning, erythema, edema, scaling/crusting, hypo/hyperpigmentation, itching, erosion, oozing/vesiculation/crusting, dryness.

In the trials for face and scalp lesions, severe stinging and/or burning at one or more lesions during light treatment was reported by at least 50% of subjects. Severe stinging and/or burning also occurred during light treatment in 9% of subjects receiving treatment for upper extremity lesions. The majority of subjects reported that all lesions treated exhibited at least slight stinging and/or burning. In trials of the face and scalp, the sensation of stinging/burning appeared to reach a plateau at 6 minutes into the treatment. Less than 3% of subjects receiving treatment for face or scalp lesions discontinued light treatment because of stinging/burning. No subjects discontinued light treatment in the trial for upper extremity lesions.

In trials for the face or scalp lesions, 99% of the active treatment group and 79% of the vehicle group experienced erythema shortly after treatment. In the trial for the upper extremity lesions, 99% of LEVULAN KERASTICK topical solution treatment group and 52% of the vehicle group experienced erythema on visit Days 2-3. Approximately 35% of LEVULAN KERASTICK topical solution group had edema, while edema occurred in <1% of the vehicle group. Both erythema and edema resolved to baseline or improved by 4 weeks after therapy for face or scalp. Edema resolved by 4 weeks and erythema resolved to baseline by 8 weeks for upper extremities.

The application of LEVULAN KERASTICK topical solution to perilesional skin resulted in stinging, burning, erythema and edema similar to treated actinic keratoses [see Warnings and Precautions (5.2)] .

Other Localized Cutaneous Adverse Experiences: Table 2depicts the incidence and severity of cutaneous adverse events in trials for the face and scalp.

TABLE 2 Post-PDT Cutaneous Adverse Events – ALA-018/ALA-019 For the Face and Scalp
 | FACE |  |  |  | SCALP
 | LEVULAN KERASTICK Topical Solution + PDT (n=139) |  | Vehicle + PDT (n=41) |  | LEVULAN KERASTICK Topical Solution + PDT (n=42) |  | Vehicle + PDT (n=21)
Degree of Severity | Mild/ Moderate | Severe | Mild/ Moderate | Severe | Mild/ Moderate | Severe | Mild/ Moderate | Severe
Scaling/Crusting | 71% | 1% | 12% | 0% | 64% | 2% | 19% | 0%
Pain | 1% | 0% | 0% | 0% | 0% | 0% | 0% | 0%
Tenderness | 1% | 0% | 0% | 0% | 2% | 0% | 0% | 0%
Itching | 25% | 1% | 7% | 0% | 14% | 7% | 19% | 0%
Edema | 1% | 0% | 0% | 0% | 0% | 0% | 0% | 0%
Ulceration | 4% | 0% | 0% | 0% | 2% | 0% | 0% | 0%
Bleeding/Hemorrhage | 4% | 0% | 0% | 0% | 2% | 0% | 0% | 0%
Hypo/hyper-pigmentation | 22% |  | 20% |  | 36% |  | 33%
Vesiculation | 4% | 0% | 0% | 0% | 5% | 0% | 0% | 0%
Pustules | 4% | 0% | 0% | 0% | 0% | 0% | 0% | 0%
Oozing | 1% | 0% | 0% | 0% | 0% | 0% | 0% | 0%
Dysesthesia | 2% | 0% | 0% | 0% | 0% | 0% | 0% | 0%
Scabbing | 2% | 1% | 0% | 0% | 0% | 0% | 0% | 0%
Erosion | 14% | 1% | 0% | 0% | 2% | 0% | 0% | 0%
Excoriation | 1% | 0% | 0% | 0% | 0% | 0% | 0% | 0%
Wheal/Flare | 7% | 1% | 0% | 0% | 2% | 0% | 0% | 0%
Skin disorder NOS | 5% | 0% | 0% | 0% | 12% | 0% | 5% | 0%

Table 3depicts the incidence of other cutaneous adverse events in Phase 3 studies for the upper extremities.

TABLE 3 Percentage of Subjects with Cutaneous Adverse Reactions by the Most Severe Grade Reported Post-Baseline – CP0108 For Upper Extremities
 | LEVULAN KERASTICK Topical Solution + PDT (N=135) |  |  | Vehicle + PDT (N=134)
Degree of Severity | Minimal/ Mild | Moderate/ Severe | Total | Minimal/ Mild | Moderate/ Severe | Total
Edema | 51% | 4% | 56% | 7% | 1% | 8%
Erythema | 35% | 65% | 100% | 63% | 12% | 75%
Hyper-pigmentation | 64% | 9% | 73% | 57% | 10% | 66%
Hypo-pigmentation | 46% | 4% | 50% | 50% | 5% | 55%
Oozing/Vesiculation/ Crusting | 36% | 5% | 41% | 8% | 2% | 10%
Scaling and Dryness | 65% | 22% | 87% | 58% | 7% | 64%
Stinging/Burning | 23% | 73% | 96% | 23% | 0% | 23%

In the trial for upper extremity lesions, itching and scabbing occurred in 8% and 4%, respectively, of the subjects in the LEVULAN KERASTICK photodynamic therapy group. No subjects in the vehicle group reported itching or scabbing.

Common (>2%, <10%) local cutaneous adverse reactions for face, scalp and upper extremities in the LEVULAN KERASTICK topical solution group included wheal, scabbing, pustules, ulceration, bleeding, tenderness and dysesthesia.

Uncommon (<2%) local cutaneous adverse reactions for face, scalp and upper extremities in the LEVULAN KERASTICK topical solution group were flaking, pain, peeling, perilesional pruritic rash, excoriation and blistering.

Common (>2%, <10%) adverse reactions not limited to the application site for upper extremities and occurring more frequently in the LEVULAN KERASTICK topical solution group than in the vehicle group were sinusitis, squamous cell carcinoma, and squamous cell carcinoma of skin.

6.2 Postmarketing Experience

The following adverse reactions have been reported during post-approval use of LEVULAN KERASTICK. Because these reactions are reported voluntarily from a population of uncertain size, it is not always possible to reliably estimate their frequency or establish a causal relationship to drug exposure.

Nervous system disorders: transient amnestic episodes

7 DRUG INTERACTIONS

There have been no formal studies of the interaction of LEVULAN KERASTICK topical solution with any other drugs, and no drug-specific interactions were noted during any of the controlled clinical trials. It is, however, possible that concomitant use of other known photosensitizing agents such as St. John’s wort, griseofulvin, thiazide diuretics, sulfonylureas, phenothiazines, sulfonamides and tetracyclines might increase the photosensitivity reaction of actinic keratoses treated with LEVULAN KERASTICK topical solution [see Warnings and Precautions (5.2)] .

8 USE IN SPECIFIC POPULATIONS

8.1 Pregnancy

Risk Summary

Limited available data with LEVULAN KERASTICK topical solution use in pregnant women are insufficient to inform a drug associated risk of adverse developmental outcomes. Animal developmental toxicology studies were not conducted with aminolevulinic acid. LEVULAN KERASTICK solution has low systemic absorption following topical administration, and the risk of maternal use resulting in fetal exposure to the drug is unknown [see Clinical Pharmacology (12.3)].

The estimated background risk of major birth defects and miscarriage for the indicated population are unknown. All pregnancies have a background risk of birth defect, loss, or other adverse outcomes. In the U.S. general population, the estimated background risk of major birth defects and miscarriage in clinically recognized pregnancies is 2% to 4% and 15% to 20%, respectively.

8.2 Lactation

Risk Summary

There are no data on the presence of LEVULAN KERASTICK topical solution in either human or animal milk, the effects on the breastfed infant or on milk production. The developmental and health benefits of breastfeeding should be considered along with the mother’s clinical need for LEVULAN KERASTICK topical solution and any potential adverse effects on the breastfeeding child from LEVULAN KERASTICK topical solution or from the underlying maternal condition.

8.4 Pediatric Use

The safety and effectiveness in pediatric patients below the age of 18 have not been established. Actinic keratosis is not a disease generally seen in the pediatric population.

8.5 Geriatric Use

Of the 512 subjects in Phase 3 clinical trials of LEVULAN KERASTICK topical solution, 63% (321/512) were 65 years old and over, while 24% (123/512) were 75 years old and over. No overall differences in safety or substantial differences in effectiveness were observed between these subjects and younger subjects, but greater sensitivity of some older individuals cannot be ruled out.

10 OVERDOSAGE

10.1 LEVULAN KERASTICK Topical Solution Overdose

In the event that the drug is ingested, monitoring and supportive care are recommended. The patient should be advised to avoid incidental exposure to intense light sources for at least 40 hours after ingestion. The consequences of exceeding the recommended topical dosage are unknown.

10.2 BLU-U Light Overdose

There is no information on overdose of blue light from the BLU-U Blue Light Photodynamic Therapy Illuminator following LEVULAN KERASTICK topical solution application.

11 DESCRIPTION

LEVULAN KERASTICK (aminolevulinic acid HCl) for topical solution, 20%, a porphyrin precursor, contains the hydrochloride salt of aminolevulinic acid (ALA), an endogenous 5-carbon aminoketone.

ALA HCl is a white to off-white, odorless crystalline solid that is very soluble in water, slightly soluble in methanol and ethanol, and practically insoluble in chloroform, hexane and mineral oil.

The chemical name for ALA HCl is 5-amino-4-oxopentanoic acid hydrochloride (MW = 167.59). The structural formula is represented below:

The LEVULAN KERASTICK for topical solution applicator is a two-component system consisting of a plastic tube containing two sealed glass ampules and an applicator tip. One ampule contains 1.5 mL of solution vehicle comprising alcohol USP (ethanol content = 48% v/v), water, laureth-4, isopropyl alcohol, and polyethylene glycol. The other ampule contains 354 mg of aminolevulinic acid HCl as a dry solid. The applicator tube is enclosed in a protective cardboard sleeve and cap. The 20% topical solution is prepared just prior to the time of use by breaking the ampules and mixing the contents by shaking the LEVULAN KERASTICK applicator. “LEVULAN KERASTICK for topical solution” refers to the drug product in its unmixed state, “LEVULAN KERASTICK topical solution” refers to the mixed drug product (in the applicator tube or after application), and “LEVULAN KERASTICK” refers to the applicator only.

12 CLINICAL PHARMACOLOGY

12.1 Mechanism of Action

Following the application of LEVULAN KERASTICK topical solution, photosensitization occurs through the metabolic conversion of aminolevulinic acid to protoporphyrin IX (PpIX), a photosensitizer, which accumulates in the skin.

When exposed to light of appropriate wavelength and energy, the accumulated photoactive porphyrins produce a photodynamic reaction, resulting in a cytotoxic process dependent upon the simultaneous presence of oxygen. The absorption of light results in an excited state of porphyrin molecules, and subsequent spin transfer from photoreactive porphyrins to molecular oxygen generates singlet oxygen, which can further react to form superoxide and hydroxyl radicals. LEVULAN KERASTICK Photodynamic Therapy of actinic keratoses is the combination of photosensitization by application of the LEVULAN KERASTICK topical solution to the lesions and subsequent illumination with BLU-U Blue Light Photodynamic Therapy Illuminator.

12.2 Pharmacodynamics

ALA does not exhibit fluorescence, while PpIX has a high fluorescence yield. Time-dependent changes in surface fluorescence have been used to determine PpIX accumulation and clearance in actinic keratoses and perilesional skin after application of the LEVULAN KERASTICK topical solution in 12 subjects. Peak fluorescence intensity was reached in 11 ± 1 hr in actinic keratoses and 12 ± 1 hr in perilesional skin. The mean clearance half-life of fluorescence for lesions was 30 ± 10 hr and 28 ± 6 hr for perilesional skin. The fluorescence in perilesional skin was similar to that in actinic keratoses. Therefore, the LEVULAN KERASTICK topical solution should only be applied to the affected skin.

12.3 Pharmacokinetics

Two human pharmacokinetic (PK) studies were conducted in subjects with minimally to moderately thick actinic keratoses on the upper extremities, having at least 6 lesions on one upper extremity and at least 12 lesions on the other upper extremity. A single dose comprising of two topical applications of LEVULAN KERASTICK topical solution (each containing 354 mg ALA HCl) were directly applied to the lesions and occluded for 3 hours prior to light treatment.

The first PK study was conducted in 29 subjects and PK parameters of ALA were assessed. The baseline-corrected mean ± SD of the maximum concentration (Cmax) of ALA was 249.9 ± 694.5 ng/mL and the median time to reach Cmax(Tmax) was 2 hr post dose. The mean ± SD exposure to ALA, as expressed by area under the concentration time curve (AUCt) was 669.9 ± 1610 ng∙hr/mL. The mean ± SD elimination half-life (T1/2) of ALA was 5.7 ± 3.9 hr.

A second PK study was conducted in 14 subjects and PK parameters of ALA and PpIX were measured. The baseline-corrected PpIX concentrations were negative in at least 50% of samples in 50% (7/14) subjects and AUC could not be estimated reliably. The baseline-corrected mean ± SD of Cmaxfor ALA and PpIX was 95.6 ± 120.6 ng/mL and 0.95 ± 0.71 ng/mL, respectively. The median Tmaxof ALA and PpIX was 2 hr post dose and 12 hr post dose, respectively. The mean AUCtof ALA was 261.1 ± 229.3 ng∙hr/mL. The mean ± SD T1/2of ALA was 8.5 ± 6.7 hr.

13 NONCLINICAL TOXICOLOGY

13.1 Carcinogenesis, Mutagenesis, Impairment of Fertility

No carcinogenicity testing has been carried out using ALA. No evidence of mutagenic effects was seen in four studies conducted with ALA to evaluate this potential. In the Salmonella-Escherichia coli/mammalian microsome reverse mutation assay (Ames mutagenicity assay), no increases in the number of revertants were observed with any of the tester strains. In the Salmonella-Escherichia coli/mammalian microsome reverse mutation assay in the presence of solar light radiation (Ames mutagenicity assay with light), ALA did not cause an increase in the number of revertants per plate of any of the tester strains in the presence or absence of simulated solar light. In the L5178Y TK± mouse lymphoma forward mutation assay, ALA was evaluated as negative with and without metabolic activation under the study conditions. PpIX formation was not demonstrated in any of these in vitro studies. In the in vivo mouse micronucleus assay, ALA was considered negative under the study exposure conditions. In contrast, at least one report in the literature has noted genotoxic effects in cultured rat hepatocytes after ALA exposure with PpIX formation. Other studies have documented oxidative DNA damage in vivo and in vitro as a result of ALA exposure.

No assessment of effects of ALA HCl on fertility has been performed in laboratory animals. It is unknown what effects systemic exposure to ALA HCl might have on fertility or reproductive function.

14 CLINICAL STUDIES

14.1 Actinic Keratoses of the Face or Scalp

LEVULAN KERASTICK for topical solution plus blue light at 6-10.9 J/cm^2, has been used to treat actinic keratoses of the face or scalp in 342 subjects in seven clinical trials. Phase 3 trials ALA-018 and ALA-019 were two, identically designed, multicenter, two-arm trials using LEVULAN KERASTICK topical solution plus illumination from the BLU-U Blue Light Photodynamic Therapy Illuminator for 1000 seconds (16 minutes and 40 seconds) for a nominal exposure of 10 J/cm^2. Subjects were excluded from these trials who had a history of cutaneous photosensitization, porphyria, hypersensitivity to porphyrins, photodermatosis, or inherited or acquired coagulation defects. A minimum of 4 and a maximum of 15 clinically typical, discrete, Grade 1 (slightly palpable actinic keratoses: better felt than seen), or Grade 2 (moderately thick actinic keratoses: easily seen and felt) target actinic keratoses were identified (see Table 5for definitions). Target lesions on the face or on the scalp, but not on both locations in the same subject, received treatment. The subjects were randomized to receive treatment either with the LEVULAN KERASTICK topical solution plus BLU-U Blue Light Photodynamic Therapy Illuminator or vehicle plus BLU-U Blue Light Photodynamic Therapy Illuminator. Subjects were randomized at a 3 to 1 LEVULAN KERASTICK topical solution to vehicle ratio. A total of 243 subjects were enrolled in two Phase 3 trials (ALA-018, ALA-019). Lesions were designated as cleared (complete response) if the lesion had completely cleared and adherent scaling plaques of actinic keratoses were no longer evident on the surface of the treated skin when palpated. The percentage of subjects in whom 75% or more of treated lesions were cleared, and the percentage of subjects in whom 100% of treated lesions were cleared (Complete Responders), for each trial 8 weeks after treatment are shown in Table 4.

TABLE 4 - Subject Responses at Week 8
 | ALA-018 |  | ALA-019
 | LEVULAN KERASTICK Topical Solution + PDT | Vehicle + PDT | LEVULAN KERASTICK Topical Solution + PDT | Vehicle + PDT
 | Subjects with >75% of AK Lesions Cleared
Total No. Subjects | 68/87 (78%) | 6/29 (21%) | 71/93 (76%) | 8/32 (25%)
Subjects with Face Lesions | 57/71 (80%) | 2/21 (10%) | 57/67 (85%) | 7/19 (37%)
Patients with Scalp Lesions | 11/16 (69%) | 4/8 (50%) | 14/26 (54%) | 1/13 (8%)
 | Complete Responders
Total No. Subjects | 60/87 (69%) | 4/29 (14%) | 59/93 (63%) | 4/32 (13%)
Subjects with Face Lesions | 49/71 (69%) | 2/21 (10%) | 47/67 (70%) | 4/19 (21%)
Subjects with Scalp Lesions | 11/16 (69%) | 2/8 (25%) | 12/26 (46%) | 0/13 (0%)

Because ALA-018 and ALA-019 had identical protocols, the combined results from the two trials are shown in the following tables. For actinic keratoses with a variety of thicknesses (excluding very thick, Grade 3 actinic keratoses which were not studied in the Phase 3 trials), LEVULAN KERASTICK topical solution plus BLU-U Blue Light Photodynamic Therapy Illuminator is more effective than vehicle plus BLU-U Blue Light Photodynamic Therapy Illuminator, but as shown in Table 5, the percentage of lesions with complete responses at 8 weeks after treatment with LEVULAN KERASTICK topical solution plus blue light illumination was lower for those lesions that were thicker at baseline. Efficacy of LEVULAN KERASTICK topical solution plus BLU-U Blue Light Photodynamic Therapy Illuminator on higher grade lesions was not studied in the Phase 3 clinical efficacy trials.

TABLE 5 Lesions Complete Responses at Week 8 for Different Lesion Grades
Lesion Grade | LEVULAN KERASTICK Topical Solution + PDT | Vehicle + PDT
Grade 1 (slightly palpable actinic keratoses: better felt than seen) | 666/756 (88%) | 122/302 (40%)
Grade 2 (moderately thick actinic keratoses: easily seen and felt) | 495/632 (78%) | 52/199 (26%)
Grade 3 (very thick and/or hyperkeratotic actinic keratoses) | 0 | 0

Those subjects who were not Complete Responders at Week 8 had retreatment of the persistent target lesions at Week 8. Among the subjects undergoing retreatment, efficacy results seen at 12 weeks after the initial treatment, i.e., at 4 weeks after the second treatment, are shown in Table 6.

TABLE 6 Complete Responders at Week 12, Among Subjects Receiving Two Treatments
 | LEVULAN KERATICK Topical Solution + PDT | Vehicle + PDT
Total No. Subjects | 24/56 (43%) | 2/49 (4%)
Subjects with Face Lesions | 21/40 (53%) | 2/31 (6%)
Subjects with Scalp Lesions | 3/16 (19%) | 0/18 (0%)

The efficacy results seen at 12 weeks after treatment, which include the results at 12 weeks for those subjects who received a single treatment as well as the results at 12 weeks for those subjects who received a second treatment at week 8, are shown in Table 7.

TABLE 7 Subject Responses at Week 12, Among Subjects Who Received One or Two Treatments
 | LEVULAN KERASTICK Topical Solution + PDT | Vehicle + PDT
 | Subjects with >75% of Actinic Keratosis Lesions Cleared
Total No. Subjects | 158/180 (88%) | 12/61 (20%)
Subjects with Face Lesions | 127/138 (92%) | 8/40 (20%)
Subjects with Scalp Lesions | 31/42 (74%) | 4/21 (19%)
 | Complete Responders
Total No. Subjects | 129/180 (72%) | 7/61 (11%)
Subjects with Face Lesions | 108/138 (78%) | 5/40 (13%)
Subjects with Scalp Lesions | 21/42 (50%) | 2/21 (10%)

Among Complete Responders at Week 8, 93% (in ALA-018) and 83% (in ALA-019) maintained complete response at Week 12. Among subjects with scalp lesions, the percentage of subjects with 100% of actinic keratosis lesions having complete response declined from Week 8 (55%) to Week 12 (50%), because there were more subjects with scalp lesions with 100% of actinic keratosis lesions cleared at Week 8 who had a recurrence of a lesion by Week 12 than there were subjects with scalp lesions who had retreatment of persistent lesions at Week 8 and who then achieved 100% of actinic keratosis lesions cleared by Week 12. Subjects did not receive follow-up past 12 weeks after the initial treatment.

Subject outcomes recorded in the two Phase 3 trials are depicted in the following flowchart, in which Complete Responders are designated clear. Seven subjects in the active treatment arm and three subjects in the vehicle treatment arm withdrew or were lost to follow-up. Three subjects in the active treatment arm were treated at baseline but did not return for evaluation until Week 12. One subject in the active treatment arm and two in the vehicle treatment arm who were not clear at Week 8 did not receive retreatment.

An open-label trial enrolled 110 subjects with 4 to 10 clinically typical, discrete actinic keratoses on the face or scalp, but not both locations. The target lesions were treated with the LEVULAN KERASTICK topical solution plus BLU-U Blue Light Photodynamic Therapy Illuminator. Any treated lesions that were not clear at Month 2 (Week 8) were re-treated. Subjects were followed monthly for 12 months. Lesions were designated as cleared if the lesion had completely cleared and adherent scaling plaques of actinic keratoses were no longer evident on the surface of the treated skin when palpated. The percentages of subjects in whom 100% of treated lesions were cleared (Complete Responders) by month, starting at Month 3 (Week 12), are shown in Figure 4. Of the 72 subjects with 100% of treated lesions cleared (Complete Responders) at Month 3, 53% had a recurrence by Month 12. A total of 748 individual lesions were treated; 539 were treated once and 209 were treated twice. At Month 3, 624 lesions (83%) were cleared. From Month 3 through Month 12 of the trial, 476 lesions (64%) remained clear. See Figure 5. Of the 624 treated lesions determined cleared at Month 3, 24% had recurred by Month 12, while 5% were lost to follow-up and their recurrence status is unknown.

14.2 Actinic Keratoses of the Upper Extremities

The safety and efficacy of LEVULAN KERASTICK topical solution plus BLU-U Blue Light Photodynamic Therapy Illuminator at 10J/cm^2to treat actinic keratoses of the upper extremities has been evaluated in a multicenter randomized, parallel-group, evaluator-blinded, vehicle-controlled trial of 269 subjects.

In this trial (CP0108), 269 subjects with 4 -15 mild to moderate actinic keratoses on the upper extremities (dorsal hand/forearm area between the elbow and the base of the fingers) were treated with LEVULAN KERASTICK topical solution and BLU-U Blue Light Photodynamic Therapy Illuminator. Subjects ranged from 45 to 90 years of age (mean 68 years) and 90% had Fitzpatrick Skin Type I, II or III. No subjects had Fitzpatrick Skin Type V or VI. Approximately 70% of subjects were male and all subjects were Caucasian.

Subjects were randomized to treatment in a 1:1 ratio to receive either LEVULAN KERASTICK topical solution or vehicle. Treatment was applied to 4-15 lesions on one dorsal hand/forearm on each subject, and occluded for the three-hour incubation period before treatment with 10 J/cm^2blue light delivered at 10 mW/cm^2. Treatment was repeated at Week 8 if any actinic keratosis lesions were present in the treatment area.

The primary endpoint was the proportion of subjects with complete clearance of all actinic keratosis lesions in the treatment area 12 weeks after initial treatment. The results of the trial are presented in Table 8.

Table 8 – Number and Percentage of Subjects with Actinic Keratosis of the Upper Extremities Achieving Complete Clearance at Week 12
 | LEVULAN KERASTICK Topical Solution + PDT | Vehicle + PDT
CP0108 | 42/135 (31%) | 17/134 (13%)

Subject outcomes recorded in the trial of the upper extremities are depicted in the following flowchart.

Subjects who achieved complete clearance at Week 12 entered a 12-month follow-up period. Subjects who received LEVULAN KERASTICK topical solution with blue light and achieved complete clearance at Week 12 in CP0108A had a recurrence rate of 58% (22/38) at 12 months, where recurrence was defined as the presence of at least one previously treated lesion in the treatment area at any visit during the 12-month follow-up period.

16 HOW SUPPLIED/STORAGE AND HANDLING

16.1 How Supplied

The LEVULAN KERASTICK for topical solution, 20%, is supplied in packs of 6 applicators. Each LEVULAN KERASTICK applicator is for single use and consists of a plastic tube containing two sealed glass ampules and an applicator tip. One ampule contains 1.5 mL of solution vehicle. The other ampule contains 354 mg of aminolevulinic acid HCl. The applicator is covered with a protective cardboard sleeve and cap.

16.2 Product Package - NDC Number

Carton of 6 LEVULAN KERASTICK for topical solution, 20% applicators 67308-101-06

16.3 Storage

Store between 20° - 25 °C (68° - 77 °F); excursions permitted to 15°- 30 °C (59° - 86 °F) [See USP Controlled Room Temperature]. The LEVULAN KERASTICK topical solution should be used immediately following preparation (dissolution). Solution application must be completed within 2 hours of preparation. An applicator that has been prepared must be discarded 2 hours after mixing (dissolving) and a new LEVULAN KERASTICK applicator used, if needed.

17 PATIENT COUNSELING INFORMATION

Advise the patient to read the FDA-approved patient labeling (Patient Information and Instructions for Use).

Transient Amnestic Episodes

Transient episodes of amnesia have been reported with LEVULAN KERASTICK in combination with BLU-U Blue Light Photodynamic Therapy Illuminator. Advise patients and their families or caregivers to contact their healthcare provider if memory impairment, confusion, or disorientation is observed [see Warnings and Precautions (5.1)].

Photosensitivity

Transient episodes of amnesia have been reported with LEVULAN KERASTICK in combination with BLU-U Blue Light Photodynamic Therapy Illuminator. Advise patients and their families or caregivers to contact their healthcare provider if memory impairment, confusion, or disorientation is observed [see Warnings and Precautions (5.2)].

Advise patients that after LEVULAN KERASTICK topical solution has been applied, the treatment site will become photosensitive and that they should avoid exposure of the photosensitive treatment sites to sunlight or bright indoor light (e.g., examination lamps, operating room lamps, tanning beds, or lights at close proximity) for 40 hours. Exposure may result in a stinging and/or burning sensation and may cause erythema and/or edema of the lesions [see Warnings and Precautions (5.2)].

Advise patients to protect treated lesions from the sun by wearing a wide-brimmed hat or similar head covering of light-opaque material, and/or a long-sleeved shirt and/or gloves. Advise patients sunscreens will not protect against photosensitivity reactions caused by visible light. It has not been determined if perspiration can spread the LEVULAN KERASTICK topical solution outside the treatment site to the eye or surrounding skin [see Warnings and Precautions (5.2)].

If for any reason the patient cannot return for blue light treatment during the prescribed period after applying LEVULAN KERASTICK topical solution, advise patients to call the doctor. Advise patient to continue to avoid exposure of the photosensitized lesions to sunlight or prolonged or intense light for at least 40 hours. If stinging and/or burning is noted, exposure to light should be reduced [see Warnings and Precautions (5.2)].

Advise patients to avoid certain medications that may enhance the phototoxic reaction to PDT [see Drug Interactions (7)] .

Common Adverse Reactions
Inform patients that treatment with LEVULAN KERASTICK topical solution plus BLU-U Blue Light Photodynamic Therapy Illuminator may result in sensitivity to light, skin irritation and local skin reactions including erythema, edema, stinging/burning, scaling, crusting, oozing, vesiculation, wheal, scabbing, pustules, ulceration, itching, erosion, hypo/hyperpigmentation, bleeding, tenderness, dysesthesia, and dryness.

LEVULAN, KERASTICK, KERASTICK KRUSHER, BLU-U, and DUSA are registered trademarks of DUSA Pharmaceuticals, Inc., a Sun Pharma company © 2020 Sun Pharmaceutical Industries, Inc. All rights reserved.

1. Manufactured by: Sun Pharmaceutical Industries, Inc.
2. Billerica, MA, 01821
3. LAB-0530AW, Revision: F

Sun Pharmaceutical Industries, Inc.

Princeton, NJ

1-877-533-3872

PATIENT INFORMATION
LEVULAN®KERASTICK®(LEV-you-lan KER-rah-stick)
(aminolevulinic acid HCl)
for topical solution, 20%

Important:LEVULAN KERASTICK is for use as an in-office treatment. LEVULAN KERASTICK treatment is given by a healthcare provider only and is not for use at home.

What is LEVULAN KERASTICK?
LEVULAN KERASTICK is a prescription medicine used on the skin (topical) with blue light treatment (BLU-U Blue Light Photodynamic Therapy or PDT) for the treatment of minimally to moderately thick actinic keratoses (AK’s) of the face, scalp, or upper arms.
It is not known if LEVULAN KERASTICK is safe and effective in children under 18 years of age.

Who should not receive LEVULAN KERASTICK treatment?
Do not receive LEVULAN KERASTICK treatment if you:

● are allergic to aminolevulinic acid HCl or to any of the ingredients in LEVULAN KERASTICK. See the end of this leaflet for a complete list of ingredients in LEVULAN KERASTICK.

● have porphyria or are allergic to porphyrins

● have a skin sensitivity to blue light

Before receiving LEVULAN KERASTICK treatment, tell your healthcare provider about all of your medical conditions, including if you:

● have blood clotting problems.

● are pregnant or plan to become pregnant. It is not known if LEVULAN KERASTICK will harm your unborn baby.

● are breastfeeding or plan to breastfeed. It is not known if LEVULAN KERASTICK passes into your breast milk. Talk to your healthcare provider about the best way to feed your baby during LEVULAN KERASTICK treatment.

Tell your healthcare provider about all of the medicines you take,including prescription and over-the-counter medicines, vitamins, and herbal supplements. LEVULAN KERASTICK and other medicines may affect each other causing side effects.

How will I receive LEVULAN KERASTICK treatment?

● LEVULAN KERASTICK treatment is received in 2 parts:

○ Your healthcare provider will apply LEVULAN KERASTICK topical solution to your skin lesions. You should not wash the treated areas before you return to your healthcare provider for blue light treatment.

○ After the prescribed amount of time you will return to your healthcare provider for blue light treatment. Call your healthcare provider if you cannot return for blue light treatment during the prescribed time after LEVULAN KERASTICK topical solution has been applied. If you cannot return for blue light treatment, avoid sunlight and bright indoor light for at least 40 hours after LEVULAN KERASTICK topical solution has been applied.

● During blue light treatment, you will likely feel tingling, stinging, prickling, or burning of the treated areas.

What should I avoid during LEVULAN KERASTICK treatment?
After LEVULAN KERASTICK topical solution is applied to your skinyou should avoid sunlight or bright indoor light (such as examination lights, operating room lights, tanning beds, or lights that are close to you) for 40 hours. During this time, the treated areas of your skin will become sensitive to light (photosensitive).
Exposure to light during this time may cause you to feel a burning or stinging sensation and may cause your treated lesions to become red or swollen. You should wear appropriate protective apparel such as a wide-brimmed hat, long sleeve shirt, and gloves to protect your treated skin from sunlight and other bright light.
Sunscreen will not protect the treated areas of your skin against sensitivity to light.

What are the possible side effects of LEVULAN KERASTICK?
LEVULAN KERASTICK may cause serious side effects, including:

● Temporary memory problems.Temporary memory problems have happened during treatment with LEVULAN KERASTICK in combination with BLU-U®Blue Light Photodynamic Therapy Illuminator. You or your family members or caregiver should call your healthcare provider right away if you develop any problems with memory, confusion, or disorientation during treatment.

● Sensitivity to light (photosensitivity).See, “What should I avoid during LEVULAN KERASTICK treatment?”

● Skin irritation.LEVULAN KERASTICK topical solution contains alcohol and may cause skin irritation if covered or bandaged for longer than 3 hours,

The common side effects of LEVULAN KERASTICK include:

● Local skin reactions including redness, swelling, stinging and burning, scaling, crusting, oozing, pustules, welts, scabbing, itching, erosion, changes in skin color, bleeding, tenderness, changes in the sense of touch, and dryness.

These are not all the possible side effects of LEVULAN KERASTICK.
Call your doctor for medical advice about side effects. You may report side effects to FDA at 1-800-FDA-1088.

General Information about LEVULAN KERASTICK
Medicines are sometimes prescribed for purposes other than those listed in a Patient Information leaflet. You can ask your pharmacist and healthcare provider for information about LEVULAN KERASTICK that is written for health professionals.

What are the Ingredients in LEVULAN KERASTICK?
Active ingredient:aminolevulinic acid HCl
Inactive ingredients:alcohol USP (ethanol content = 48% v/v), water, laureth-4, isopropyl alcohol, polyethylene glycol
Manufactured by:
Sun Pharmaceutical Industries, Inc., Billerica, MA 01821
For more information call 1-877-533-3872
www.levulanhcp.com

This Patient Information has been approved by the U.S. Food and Drug Administration.

Revised: 01/2020.

PM-US-LEV-0389 LAB-0529 REV E

PACKAGE LABEL

LEVULAN®KERASTICK®
(aminolevulinic acid HCl) for Topical Solution, 20%
SINGLE USE APPLICATOR 1.5 mL
NDC 67308-101-01
A
↑
CRUSH
HERE
↓
A
LOT NO.:
EXP. DATE:
B
↑
CRUSH
HERE
↓
B
MANUFACTURED BY:
Sun Pharmaceutical Industries, Inc.
Billerica, MA 01821
LAB-0528 AW REV F

NDC 67308-101-06
LEVULAN®
KERASTICK®
(aminolevulinic acid HCl)
for Topical Solution, 20%
6 SINGLE USE APPLICATORS/1.5 ML EACH
FOR TOPICAL USE ONLY
NOT FOR USE IN EYES
FOR ADMINISTRATION BY HEALTH PROFESSIONAL ONLY
RX Only
Each applicator contains:
Active Ingredient: 354mg aminolevulinic acid HCl
Inactive Ingredients: Alcohol, USP (ethanol content=48%v/v), Water, laureth-4, isopropyl alcohol and polyethylene glycol.
Usual Dose:For indications, dosage, precautions, etc., see enclosed package insert.
Store between 20°– 25°C (68°-77°F), excursions permitted to 15°– 30°C (59° – 86°F).
[See USP Controlled Room Temperature]
Use and discard within two hours after activation.
Sun Pharmaceutical Industries, Inc.
Billerica, MA 01821
1-877-533-3872 or
1-978-657-7500
LAB-1451 AW Rev F

6 SINGLE USE APPLICATORS, 1.5 ML EACH
Carefully follow the step by step directions provided in the package insert to prepare Levulan®Kerastick®for application. Please note the locations of the crush points “A” and “B” which are indicated by the red diamonds “♦” on each Kerastick®.

NDC 67308-101-01
Levulan®Kerastick®
(aminolevulinic acid HCl) for Topical Solution, 20%
SINGLE USE APPLICATOR 1.5 ML
LOT NO.:
EXP. DATE:
SAMPLE: NOT FOR SALE
Manufactured By:
Sun Pharmaceutical Industries, Inc.
Billerica, MA 01821
LAB-1411 REV.: C

NDC 67308-101-02
Levulan® Kerastick®
(aminolevulinic acid HCl) for Topical Solution, 20%
2 SINGLE USE APPLICATORS, 1.5 mL EACH
SAMPLE
NOT FOR SALE
For Topical Use Only
Not For Use in Eyes
FOR ADMINISTRATION BY HEALTH PROFESSIONAL ONLY
Rx only
Carefully follow the step by step directions provided in the package to prepare Levulan®Kerastick®for application. Please note the locations of the crush points "A" and "B" which are indicated by the red diamonds "♦" on each Kerastick®.
CAT. NO.:
LOT NO.:
EXP. DATE:
Sun Pharmaceutical Industries, Inc.
Billerica, MA 01821
1-877-533-3872
LAB-1462AW REV. C
Each applicator contains:
Active Ingredient: 354mg aminolevulinic acid HCl
Inactive Ingredients: Alcohol, USP (ethanol content-48% v/v), water, laureth-4, isopropyl alcohol, and polyethylene glycol.
Usual Dose:
For indications, dosage, precautions, etc., see enclosed package insert.
Store between 20°25°C (68°-77°F); excursions permitted to 15°-30°C (59°-86°F)
[See USP Controlled Room Temperature]
Use and discard within two hours after activation.